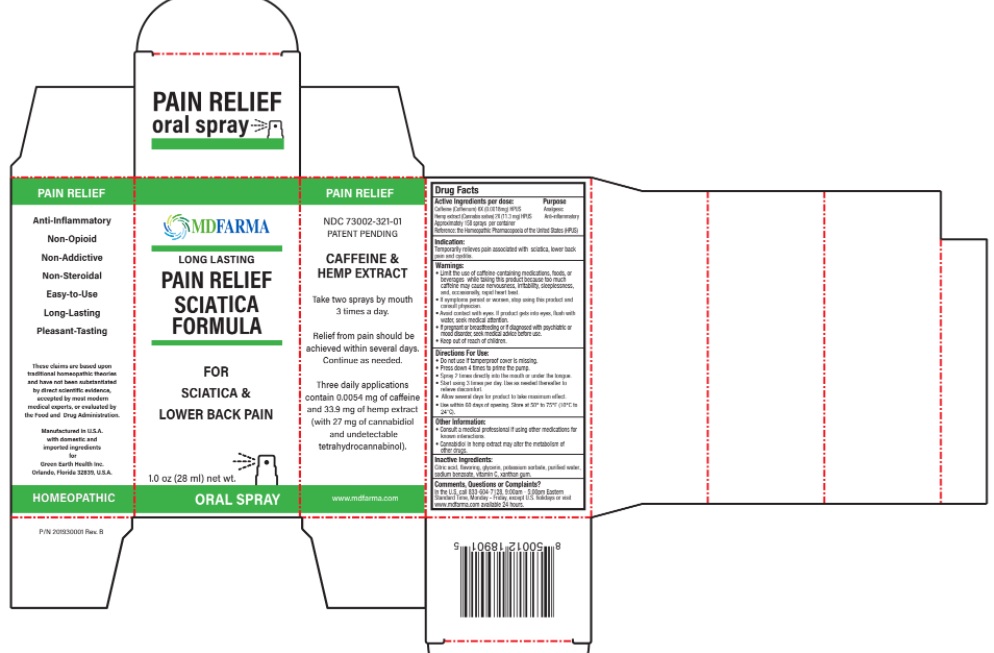 DRUG LABEL: PAIN RELIEF CAFFEINE AND HEMP
NDC: 73002-321 | Form: SPRAY
Manufacturer: Green Earth Health Inc.
Category: homeopathic | Type: HUMAN OTC DRUG LABEL
Date: 20250723

ACTIVE INGREDIENTS: CAFFEINE CITRATE 6 [hp_X]/1 mL; CANNABIS SATIVA SUBSP. SATIVA FLOWERING TOP 2 [hp_X]/1 mL
INACTIVE INGREDIENTS: ANHYDROUS CITRIC ACID; GLYCERIN; SIRAITIA GROSVENORII FRUIT; TEA LEAF; POTASSIUM SORBATE; WATER; SODIUM BENZOATE; ASCORBIC ACID; XANTHAN GUM

Drug Facts

Active Ingredients Purpose

Caffeine (Coffeinum) 6X (0.0018mg) HPUS Analgesic
Hemp extract (Cannabis sativa) 2X (11.3 mg) HPUS Anti-inflammatory

Approximately 158 sprays per container

Reference: the Homeopathic Pharmacopoeia of the United States (HPUS)

Indication:

Temporarily relieves pain associated with sciatica, lower back pain and cystitis

Warnings:

• Limit the use of caffeine-containing medications, foods, or beverages while taking this product because too much caffeine may cause nervousness, irritability, sleeplessness, and, occasionally, rapid heart beat.
• If symptoms persist or worsen, stop using this product and consult physician.
• Avoid contact with eyes. If product gets into eyes, flush with water, seek medical attention.
• If pregnant or breastfeeding or if diagnosed with psychiatric or mood disorder, seek medical advice before use.
• Keep out of reach of children.

Directions For Use:

- Do not use if tamperproof cover is missing
- Press down 4 times to prime the pump.
- Spray 2 times directly into the mouth or under the tongue.
- Start using 3 times per day. Use as needed thereafter to relieve discomfort.
- Allow several days for product to take maximum effect.
- Use within 60 days from opening. Store at 50° to 75°F (10°C to 24°C)

Other Information:

- Consult a medical professional if using other medications for known interactions.
- Cannabidiol in hemp extract may alter the metabolism of other drugs.

Inactive Ingredients:

Citric acid, flavoring, glycerin, potassium sorbate, purified water, sodium benzoate, vitamin C, xanthan gum